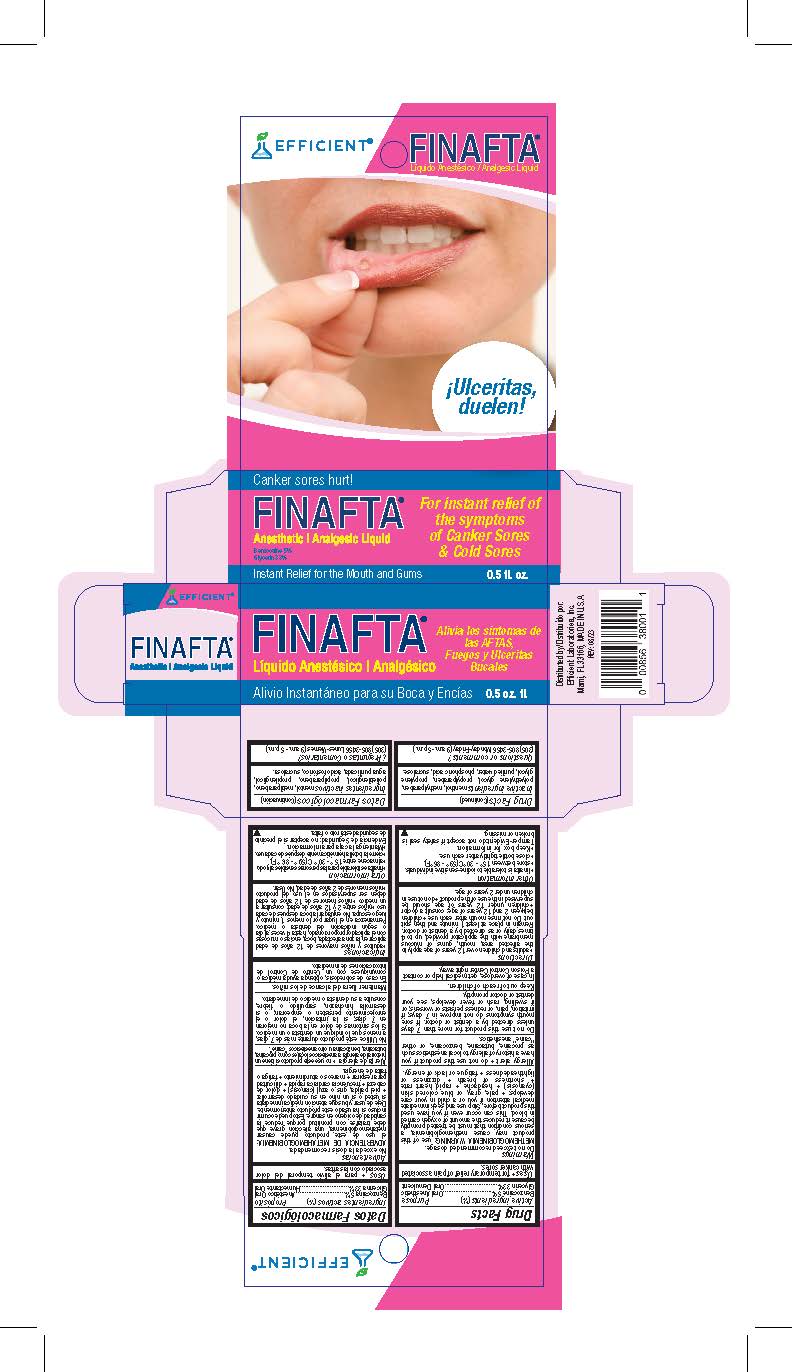 DRUG LABEL: Finafta
NDC: 58593-783 | Form: LIQUID
Manufacturer: Efficient Laboratories Inc.
Category: otc | Type: HUMAN OTC DRUG LABEL
Date: 20251014

ACTIVE INGREDIENTS: BENZOCAINE 5 mg/100 mL; GLYCERIN 33 mg/100 mL
INACTIVE INGREDIENTS: PROPYLPARABEN; POLYETHYLENE GLYCOL 1000; PHOSPHORIC ACID; MENTHOL; SUCRALOSE; METHYLPARABEN; PROPYLENE GLYCOL; WATER

Finafta

Active Ingredients: (%) Purpose

Benzocaine USP 5%..................Oral Anesthetic

Glycerin 33% .........................Oral Demulcen

Purpose

Oral Anesthetic

Oral Demulcen

Uses

For temporary relief of pain associated with canker sores

Warnings

Do not exceed recommended dosage

Methemoglobinemia warning: Use of this product may cause methemoglobinemia, a serious condition that must be treated promptly because it reduces the amount of oxygen carried in the blood. This can occur even if you have used this product before. Stop use and seek immediate medical attention if you or a child in your care develops:

- pale, gray, or blue colored skin (cyanosis)
- headache
- rapid heart rate
- shortness of breath
- dizziness or lightheadedness
- fatigue or lack of energy

Allergy alert

- do not use this product if you have a history of allergy to local anesthetics such as procaine, butacaine, benzocaine, or other "caine" anesthetics.

Do not use this product for more than 7 days unless directed by a dentist or doctor. If sore mouth symptoms do not improve in 7 days; if irritation, pain, or redness persists or worsens; or if swelling, rash or fever develops, see your dentist or doctor promptly.

Keep out of reach of children. In case of accidental overdose: Get medical help or contact a Poison Control Center right away.

Directions

•adults and children over 12 years of age apply to the affected area, mouth, gums or mucous membrane with the applicator provided, up to 4 times daily or as directed by a dentist or doctor. Remain in place at least 1 minute and then spit out. Do not rinse mouth after each use • Children between 2 and 12 years of age: consult a doctor •children under 12 years of age should be supervised in the use of the product •do not use in children under 2 years of age.

Questions or comments?

305-805-3456

Monday-Friday (9 a.m. - 5 p.m. EST)

www.efficientlabs.com

Inactive Ingredients:

menthol, methylparaben, polyethylene glycol, propylparaben, propylene glycol, purified water, phosphoric acid, sucralose.

Other Information

• finafta is tolerable to iodine-sensitive individuals.
• store between 15° - 30°C (59° - 86°F).
• close bottle tightly after each use.
• Keep box for information.
Tamper-Evident:do not accept if safety seal is broken or missing.